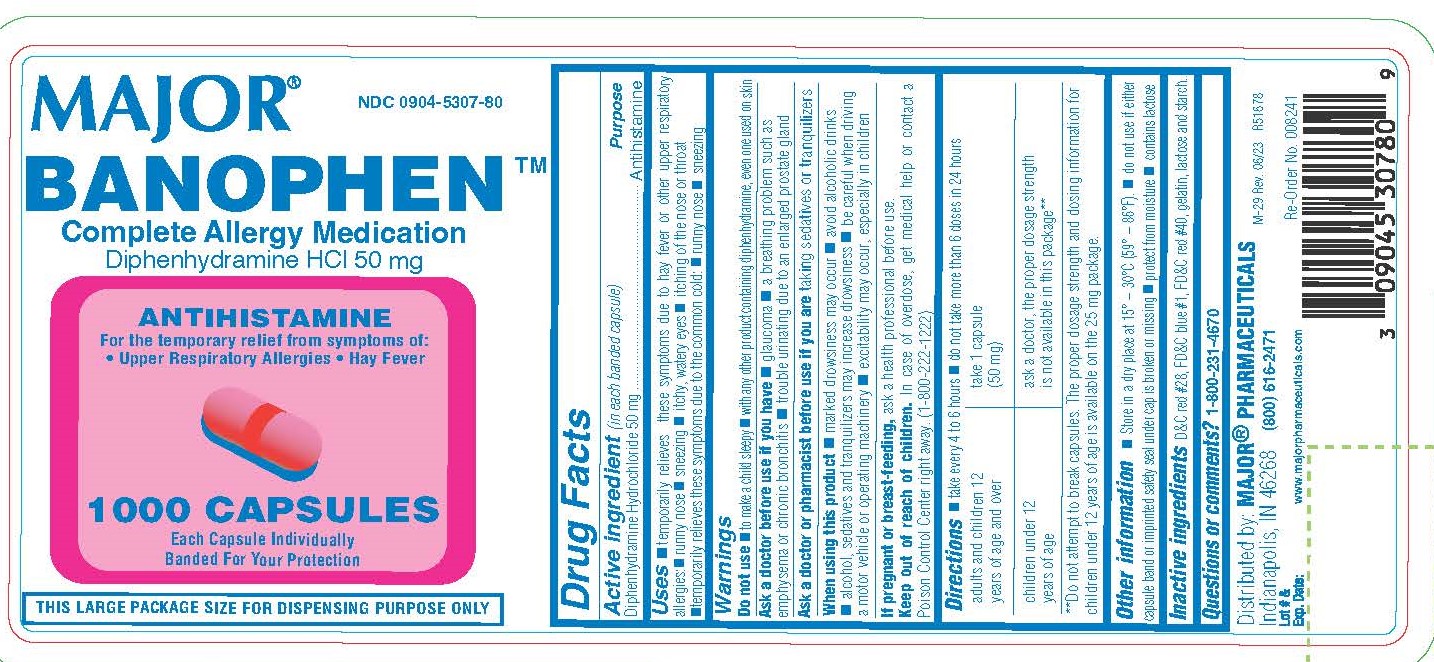 DRUG LABEL: Banophen
NDC: 0904-5307 | Form: CAPSULE
Manufacturer: Major Pharmaceuticals
Category: otc | Type: HUMAN OTC DRUG LABEL
Date: 20260220

ACTIVE INGREDIENTS: DIPHENHYDRAMINE HYDROCHLORIDE 50 mg/1 1
INACTIVE INGREDIENTS: D&C RED NO. 28; FD&C BLUE NO. 1; FD&C RED NO. 40; GELATIN; LACTOSE MONOHYDRATE; STARCH, CORN

0836-Major(100C/1000C)

Active Ingredient (in each banded capsule)

Diphenhydramine Hydrochloride 50 mg

Purpose

Antihistamine

Use

Temporarily relieves these symptoms due to hay fever or other upper respiratory allergies

- runny nose
- sneezing
- itchy, watery eyes
- itchy throat and nose
- Temporarily relieves these symptoms due to the common cold
  - runny nose
  - sneezing

Do not use

- to make a child sleepy
- with any other product containing diphenhydramine, even one used on skin

Do not use

- to make a child sleepy
- with any other product containing diphenhydramine, even one used on skin

Ask a doctor before use if you have

- glaucoma
- a breathing problem such as emphysema or chronic bronchitis
- trouble urinating due to an enlarged prostate gland

Ask a doctor or pharmacist

before use if you are taking sedatives or tranquilizers

When using this product

- marked drowsiness may occur
- avoid alcoholic drinks
- alcohol, sedatives, and tranquilizers may increase drowsiness
- be careful when driving a motor vehicle or operating machinery
- excitability may occur, especially in children

If pregnant or breast-feeding

ask a health professional before use.

KEEP OUT OF REACH OF CHILDREN

In case of overdose, get medical help or contact a Poison Control Center right away.

Directions

- Take every 4-6 hours
- Do not take more than 6 doses in 24 hours

adults and children 12 years of age and over | Take 1 capsule (50 mg)
children under 12 years of age | ask a doctor, the proper dosage strength is not available in this package**
**Do not attempt to break capsules. The proper dosage strength and dosing information for children under 12 years of age is available on the 25 mg package.

Other Information

- Store in a dry place at 15° – 30°C (59° – 86°F).
- Do not use if either capsule band or imprinted safety seal under cap is broken or missing
- Protect from moisture
- Contains lactose

Inactive Ingredients

D&C Red #28, FD&C Blue #1, FD&C Red #40, Gelatin, Lactose and Starch.

Questions?

Questions or comments?1-800-231-4670

Distributed by: MAJOR® PHARMACEUTICALS

Indianapolis, IN 46268

(800) 616-2471

www.majorpharmaceuticals.com

PACKAGE LABEL.PRINCIPAL DISPLAY PANEL

Major

NDC 0904-5307-80

BENOPHEN

Complete Allergy Medication

Diphenhydramine HCl 50 mg

ANTIHISTAMINE
For the temporary relief from symptoms of:
• Upper Respiratory Allergies • Hay Fever

1000 CAPSULES

Each Capsule Individually Banded For Your Protection

THIS LARGE PACKAGE SIZE FOR DISPENSING PURPOSE ONLY